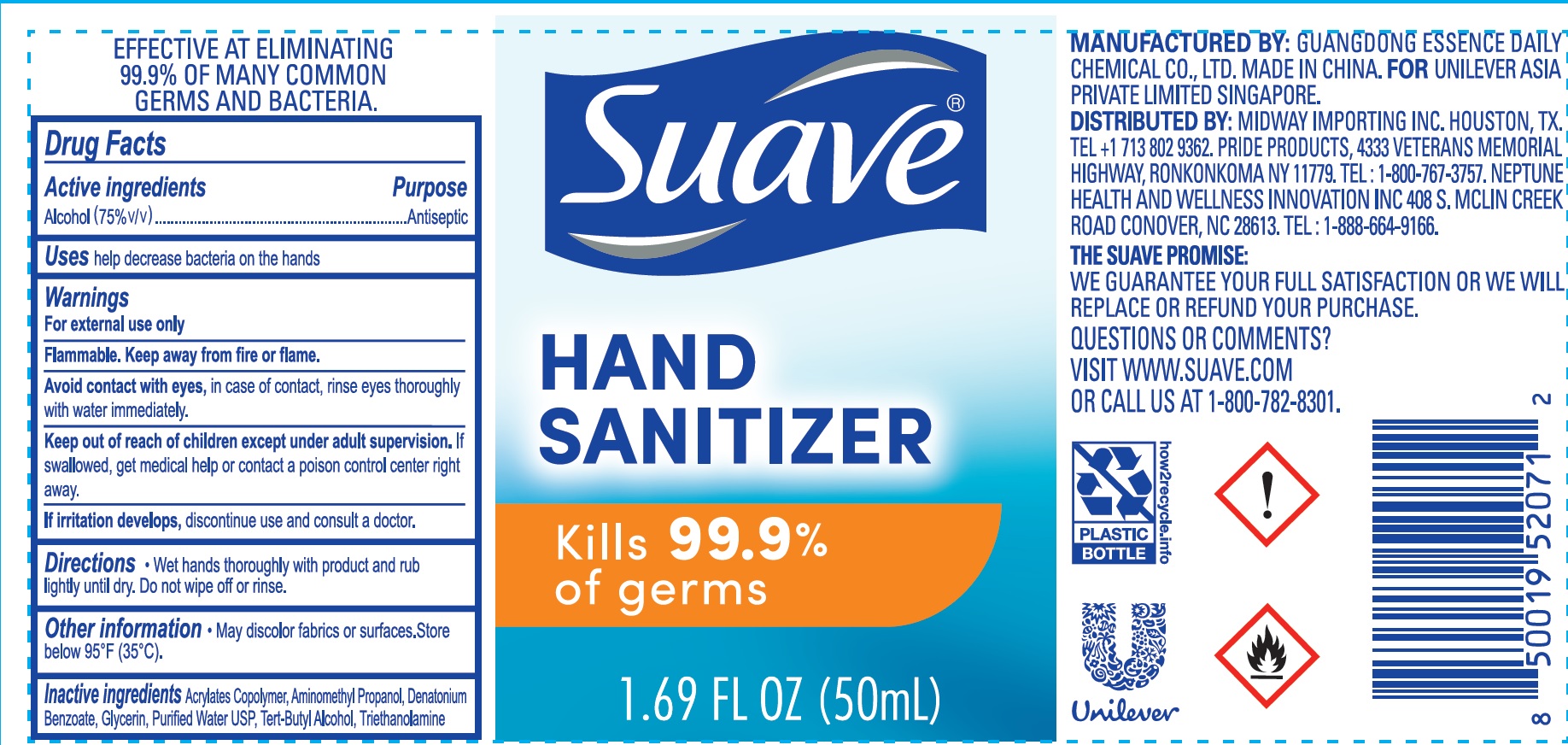 DRUG LABEL: Suave Hand Sanitizer
NDC: 73931-018 | Form: GEL
Manufacturer: Guangdong Essence Daily Chemical Co., Ltd
Category: otc | Type: HUMAN OTC DRUG LABEL
Date: 20200827

ACTIVE INGREDIENTS: ALCOHOL 75 mL/100 mL
INACTIVE INGREDIENTS: WATER; GLYCERIN; TROLAMINE; AMINOMETHYLPROPANOL; DENATONIUM BENZOATE; TERT-BUTYL ALCOHOL

Active ingredient

Alcohol 75% v/v

purpose

antiseptic

Use

help decrease bacteria on the hands

Warnings

For external use only.

Flammable, Keep away from fire or flame.

Avoid contact with eyes, in case of contact, rinse eyes thoroughly with water immediately.

If irritationdevelops，Discontinue use and consult a doctor.

Keep out of reach of children.

If swallowed, get medical help or contact a Poison Control Center right away.

Directions

- Wet hands thoroughly with product and rub lightly until dry. Do not wipe off or rinse.

Inactive ingredients

Purified Water USP, Acrylates Copolymer, Glycerin, Triethanolamine, Aminomethyl Propanol, Denatonium Benzoate, Tert-butyl Alcohol

Other information

- May discolor fabrics or urfaces.
- Store below 95℉ (35℃).